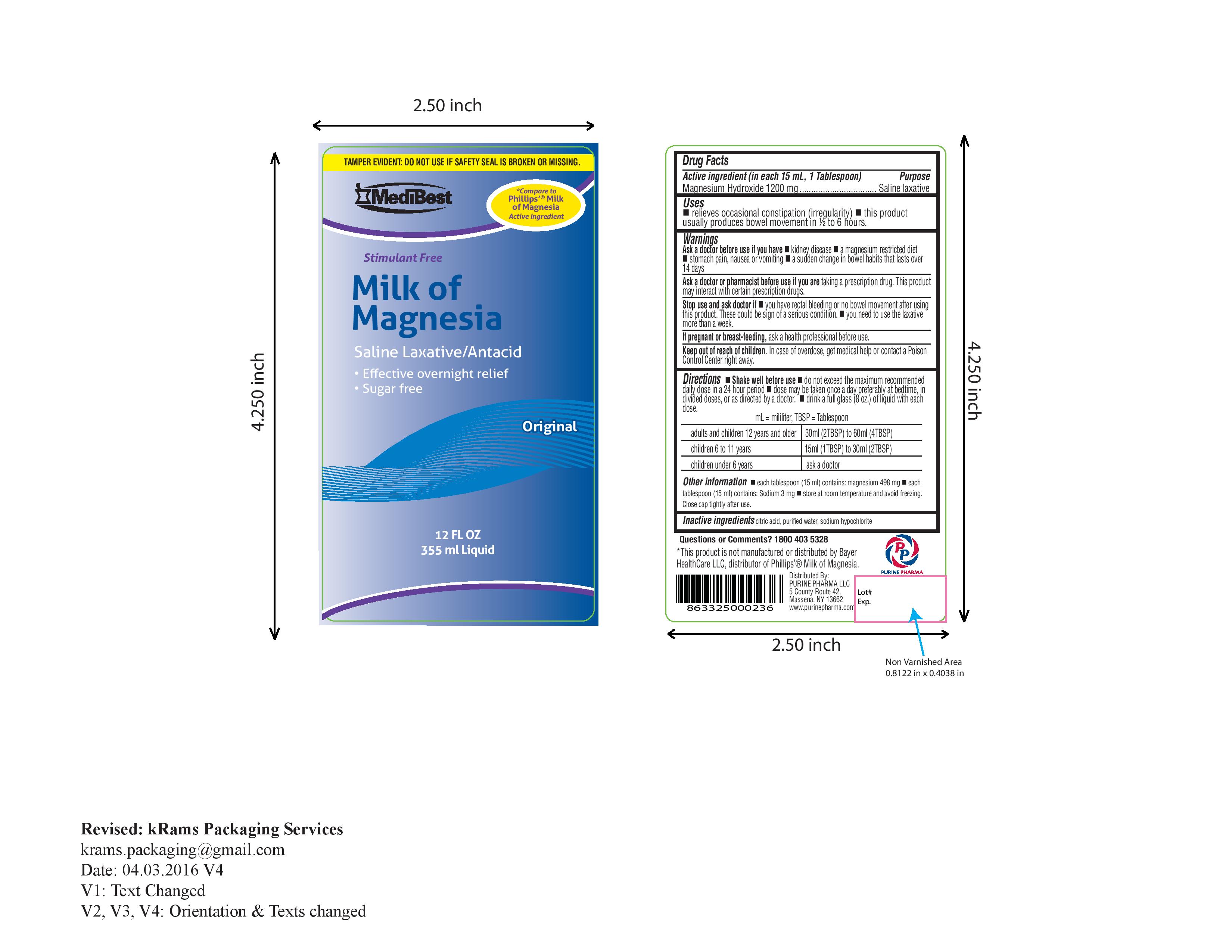 DRUG LABEL: Medibest Milk of Magnesia
NDC: 58599-058 | Form: LIQUID
Manufacturer: Purine Pharma LLC
Category: otc | Type: HUMAN OTC DRUG LABEL
Date: 20160912

ACTIVE INGREDIENTS: MAGNESIUM HYDROXIDE 1200 mg/15 mL
INACTIVE INGREDIENTS: WATER; SODIUM HYPOCHLORITE

Medibest Milk of Magnesia

Drug Facts

Active ingredient (in each 15 mL Tablespoon) Purpose

Magnesium hydroxide 1200 mg...............…………..........Saline laxative

PURPOSE

Saline laxative

Use

Use relieves occasional constipation (irregularity). This product usually produces bowel movement in ½ to 6 hours.

Warnings

Ask a doctor before use if you have

● kidney disease
● a magnesium-restricted diet
● stomach pain, nausea, or vomiting
● a sudden change in bowel habits that lasts over 14 days

Ask a doctor or pharmacist before use if you are taking a prescription drug. This product may interact with certain prescription drugs.

Stop use and ask a doctor if

● you have rectal bleeding or no bowel movement after using this product. These could be signs of a serious condition.

● you need to use a laxative for more than 1 week

PREGNANCY OR BREAST FEEDING

If pregnant or breast-feeding, ask a health professional before use.

Keep out of reach of children. In case of overdose, get medical help or contact a Poison Control Center right away.

Directions

● do not exceed the maximum recommended daily dose in a 24 hour period

● dose may be taken once a day preferably at bedtime, in divided doses, or as directed by a doctor.

- Drink a full glass (8 oz) of liquid with each dose.

● mL = milliliter; TBSP = Tablespoon

adults and children 12 years and older | 30 mL (2 TBSP) to 60 mL (4 TBSP)
children 6 to 11 years | 15 mL (1 TBSP) to 30 mL (2 TBSP)
children under 6 years | ask a doctor

Other information

● each tablespoon (15 mL) contains: magnesium 500 mg

● each tablespoon (15 mL) contains: Sodium 3mg

● store at room temperature and avoid freezing. Close cap tightly after use.

Inactive ingredients: Citric acid, purified water, sodium hypochlorite

Questions or comments? 1-800-403-5328